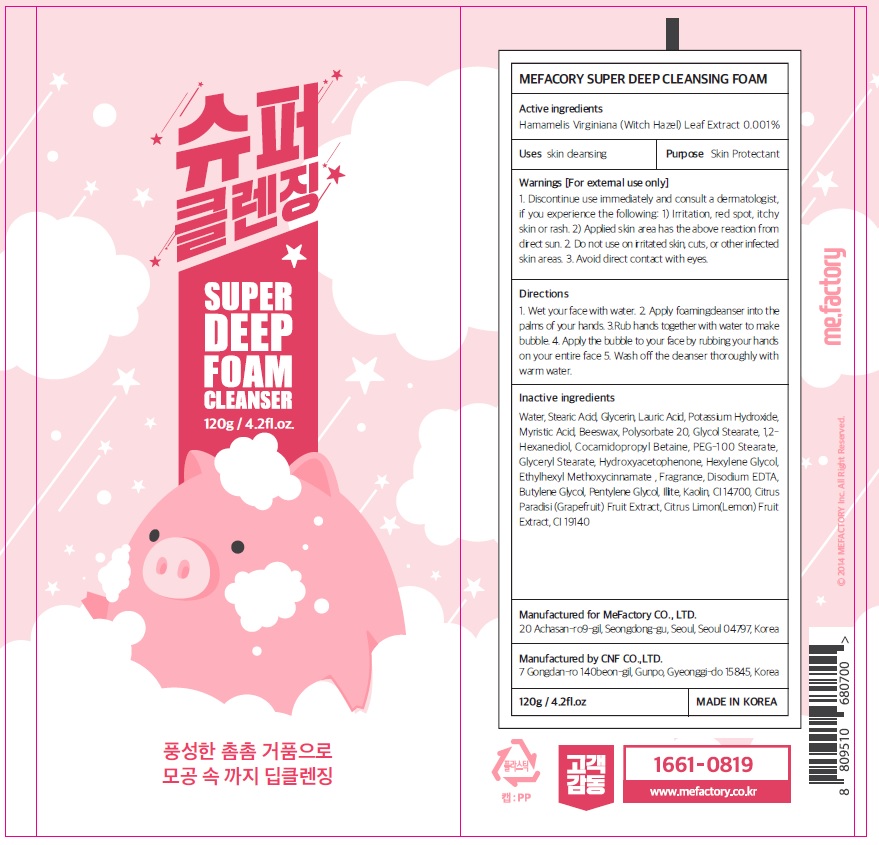 DRUG LABEL: Mefactory Super Deep Cleansing Foa m
NDC: 70908-200 | Form: CREAM
Manufacturer: MeFactory Co., Ltd.
Category: otc | Type: HUMAN OTC DRUG LABEL
Date: 20180102

ACTIVE INGREDIENTS: Witch Hazel 0.001 g/120 g
INACTIVE INGREDIENTS: WATER; Glycerin

ACTIVE INGREDIENT

Active ingredients: Hamamelis Virginiana (Witch Hazel) Leaf Extract 0.001%

INACTIVE INGREDIENT

Inactive ingredients: Water, Stearic Acid, Glycerin, Lauric Acid, Potassium Hydroxide, Myristic Acid, Beeswax, Polysorbate 20, Glycol Stearate, 1,2-Hexanediol, Cocamidopropyl Betaine, PEG-100 Stearate, Glyceryl Stearate, Hydroxyacetophenone, Hexylene Glycol, Ethylhexyl Methoxycinnamate , Fragrance, Disodium EDTA, Butylene Glycol, Pentylene Glycol, Illite, Kaolin, CI 14700 , Citrus Paradisi (Grapefruit) Fruit Extract, Citrus Limon (Lemon) Fruit Extract, CI 19140

PURPOSE

Purpose: Skin Protectant

WARNINGS

Warnings: For external use only 1. Discontinue use immediately and consult a dermatologist, if you experience the following: 1) Irritation, red spot, itchy skin or rash 2) Applied skin area has the above reaction from direct sun. 2. Do not use on irritated skin, cuts, or other infected skin areas. 3. Avoid direct contact with eyes

KEEP OUT OF REACH OF CHILDREN

Uses

Uses: Skin cleansing

Directions

Directions: 1. Wet your face with water 2. Apply foaming cleanser into the palms of your hands 3.Rub hands together with water to make bubble 4. Apply the bubble to your face by rubbing your hands on your entire face 5. Wash off the cleanser thoroughly with warm water